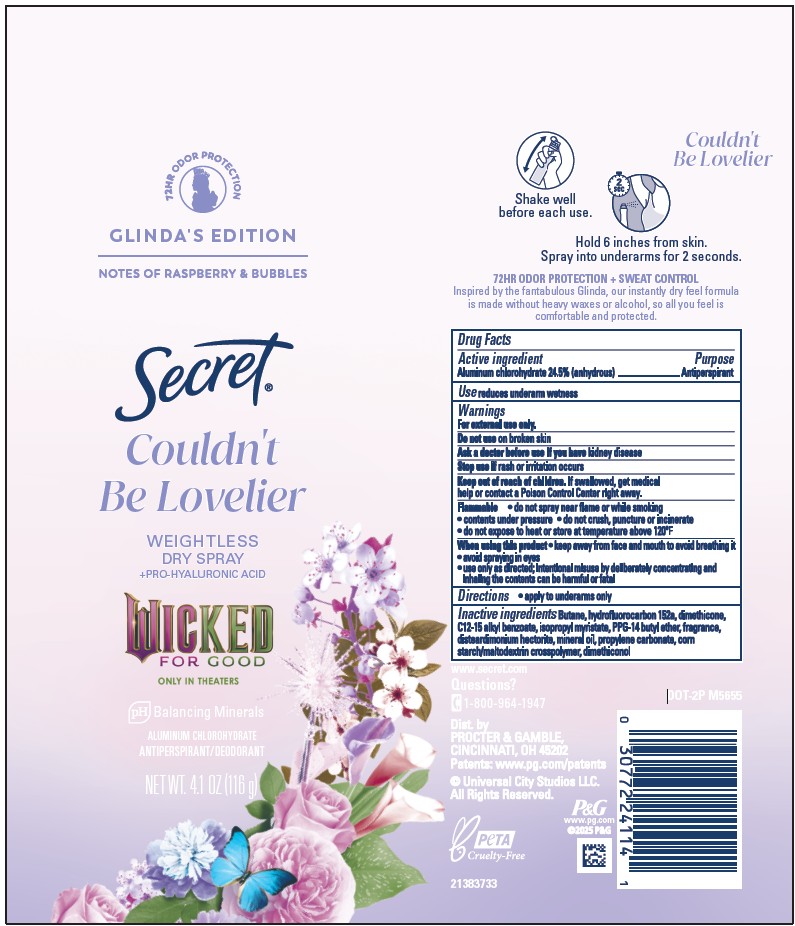 DRUG LABEL: Secret Couldnt Be Lovelier Weightless Dry Wicked for Good
NDC: 84126-217 | Form: AEROSOL, SPRAY
Manufacturer: The Procter & Gamble Manufacturing Company
Category: otc | Type: HUMAN OTC DRUG LABEL
Date: 20260127

ACTIVE INGREDIENTS: ALUMINUM CHLOROHYDRATE 24.5 g/100 g
INACTIVE INGREDIENTS: DIMETHICONE; MINERAL OIL; DIMETHICONOL (100000 CST); BUTANE; HYDROFLUOROCARBON 152A; C12-15 ALKYL BENZOATE; DISTEARDIMONIUM HECTORITE; PROPYLENE CARBONATE; ISOPROPYL MYRISTATE; PPG-14 BUTYL ETHER

Secret Couldn't Be Lovelier Weightless Dry Wicked for Good

Drug Facts

Active ingredient

Aluminum chlorohydrate 24.5% (anhydrous)

Purpose

Antiperspirant

Use

- reduces underarm wetness

Warnings

For external use only.

Do not use on broken skin

Ask a doctor before use if you have kidney disease

Stop use if rash or irritation occurs

Keep out of reach of children. If swallowed, get medical help or contact a Poison Control Center right away.

When using this product

keep away from face and mouth to avoid breathing it

avoid spraying in eyes

use only as directed; intentional misuse by deliberately concentrating and inhaling the contents can be harmful or fatal

SAFE HANDLING WARNING

Flammable

do not spray near flame or while smoking

contents under pressure
do not crush, puncture or incinerate

do not expose to heat or store at temperature above 120ºF

Directions

- apply to underarms only

Inactive ingredients

Butane, hydrofluorocarbon 152A, dimethicone, C12-15 alkyl benzoate, isopropyl myristate, PPG-14 butyl ether, fragrance, disteardimonium hectorite,mineral oil, propylene carbonate, corn starch/maltodextrin crosspolymer, dimethiconol

Questions?

1-800-964-1947

Dist. by PROCTER & GAMBLE,
CINCINNATI, OH 45202.

PRINCIPAL DISPLAY PANEL - 116 g Can

GLINDA'S EDITION

SECRET

COULDN'T BE LOVELIER

Weightless

DRY SPRAY

+PRO-HYALURONIC ACID

WICKED

FOR GOOD

ALUMINUM CHLOROHYDRATE

ANTIPERSPIRANT / DEODORANT

NET WT. 4.1 OZ (116 g)